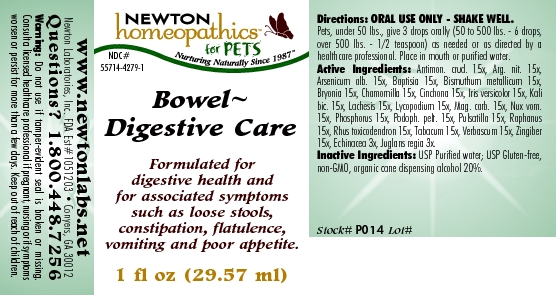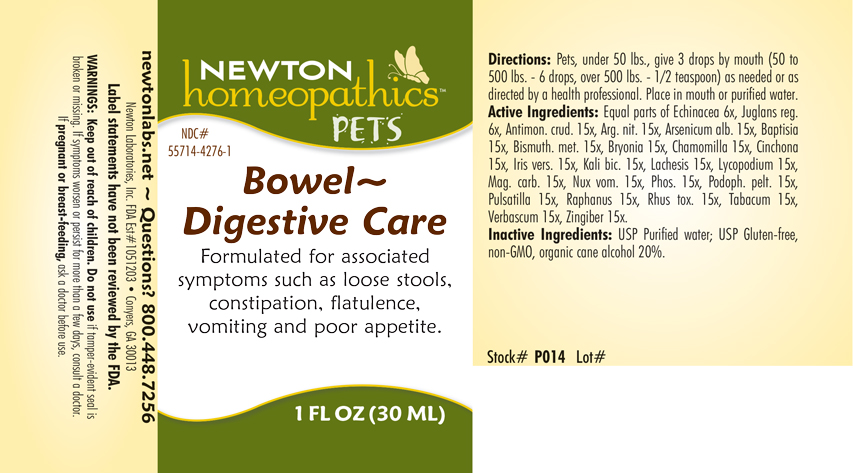 DRUG LABEL: Bowel - Digestive Care
NDC: 55714-4279 | Form: LIQUID
Manufacturer: Newton Laboratories, Inc.
Category: homeopathic | Type: OTC ANIMAL DRUG LABEL
Date: 20190114

ACTIVE INGREDIENTS: Antimony Trisulfide 15 [hp_X]/1 mL; Silver Nitrate 15 [hp_X]/1 mL; Arsenic Trioxide 15 [hp_X]/1 mL; Baptisia Tinctoria 15 [hp_X]/1 mL; Bismuth 15 [hp_X]/1 mL; Bryonia Alba Root 15 [hp_X]/1 mL; Matricaria Recutita 15 [hp_X]/1 mL; Cinchona Officinalis Bark 15 [hp_X]/1 mL; Iris Versicolor Root 15 [hp_X]/1 mL; Potassium Dichromate 15 [hp_X]/1 mL; Lachesis Muta Venom 15 [hp_X]/1 mL; Lycopodium Clavatum Spore 15 [hp_X]/1 mL; Magnesium Carbonate 15 [hp_X]/1 mL; Strychnos Nux-vomica Seed 15 [hp_X]/1 mL; Phosphorus 15 [hp_X]/1 mL; Podophyllum 15 [hp_X]/1 mL; Pulsatilla Vulgaris 15 [hp_X]/1 mL; Radish 15 [hp_X]/1 mL; Toxicodendron Pubescens Leaf 15 [hp_X]/1 mL; Tobacco Leaf 15 [hp_X]/1 mL; Verbascum Thapsus 15 [hp_X]/1 mL; Ginger 15 [hp_X]/1 mL; Echinacea, Unspecified 3 [hp_X]/1 mL; Juglans Regia Leaf 3 [hp_X]/1 mL
INACTIVE INGREDIENTS: Alcohol

Bowel - Digestive Care

INDICATIONS & USAGE SECTION

Bowel - Digestive Care Formulated for associated symptoms such as loose stools, constipation, flatulence, vomiting and poor appetite.

DOSAGE & ADMINISTRATION SECTION

Pets, under 50 lbs., give 3 drops by mouth (50 to 500 lbs. - 6 drops, over 500 lbs. - 1/2 teaspoon) as needed or as directed by a health professional. Place in mouth or purified water.

OTC - ACTIVE INGREDIENT SECTION

Equal parts of Echinacea 6x, Juglans regia 6x, Antimon. crud. 15x, Arg. nit. 15x, Arsenicum alb. 15x, Baptisia 15x, Bismuthum metallicum 15x, Bryonia 15x, Chamomilla 15x, Cinchona 15x, Iris versicolor 15x, Kali bic. 15x, Lachesis 15x, Lycopodium 15x, Mag. carb. 15x, Nux vom.15x, Phosphorus 15x, Podoph. pelt. 15x, Pulsatilla 15x, Raphanus 15x, Rhus toxicodendron 15x, Tabacum 15x, Verbascum 15x, Zingiber 15x.

OTC - PURPOSE SECTION

Formulated for associated symptoms such as loose stools, constipation, flatulence, vomiting and poor appetite.

INACTIVE INGREDIENT SECTION

Inactive Ingredients: USP Purified Water; USP Gluten-free, non-GMO, organic cane alcohol 20%.

QUESTIONS SECTION

newtonlabs.net - Questions? 1.800.448.7256 Newton Laboratories, Inc. FDA Est # 1051203 - Conyers, GA 30013

WARNINGS SECTION

Warning: Keep out of reach of children. Do not use if tamper-evident seal is broken or missing. If symptoms worsen or persist for more than a few days, consult a doctor. If pregnant or breast feeding, ask a doctor before use.

OTC - PREGNANCY OR BREAST FEEDING SECTION

If pregnant or breast feeding, ask a doctor before use.

OTC - KEEP OUT OF REACH OF CHILDREN SECTION

Keep out of reach of children.